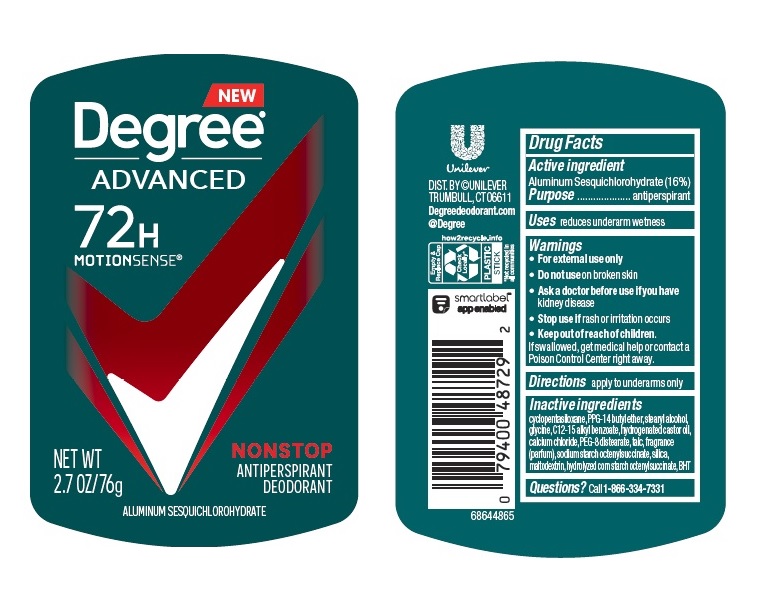 DRUG LABEL: Degree
NDC: 64942-1937 | Form: STICK
Manufacturer: Conopco Inc. d/b/a/ Unilever
Category: otc | Type: HUMAN OTC DRUG LABEL
Date: 20241108

ACTIVE INGREDIENTS: ALUMINUM SESQUICHLOROHYDRATE 16 g/100 g
INACTIVE INGREDIENTS: GLYCINE; ALKYL (C12-15) BENZOATE; HYDROGENATED CASTOR OIL; CALCIUM CHLORIDE; CYCLOMETHICONE 5; PEG-8 DISTEARATE; TALC; SILICON DIOXIDE; BUTYLATED HYDROXYTOLUENE; MALTODEXTRIN; PPG-14 BUTYL ETHER; STEARYL ALCOHOL

Degree Advanced Nonstop 72H Antiperspirant Deodorant

Drug Facts

Active ingredient

Aluminum Sesquichlorohydrate (16%)

Purpose

antiperspirant

Uses

reduces underarm wetness

• Keep out of reach of children.

If swallowed, get medical help or contact a Poison Control Center right away.

Directions

apply to underarms only

Inactive ingredients

Cyclopentasiloxane, PPG-14 Butyl Ether, Stearyl Alcohol, Glycine, C12-15 Alkyl Benzoate, Hydrogenated Castor Oil, Calcium Chloride, PEG-8 Distearate, Talc, Fragrance (Parfum), Sodium Starch Octenylsuccinate, Silica, Maltodextrin, Hydrolyzed Corn Starch Octenylsuccinate, BHT.

Questions?

Call toll-free 1-866-334-7331